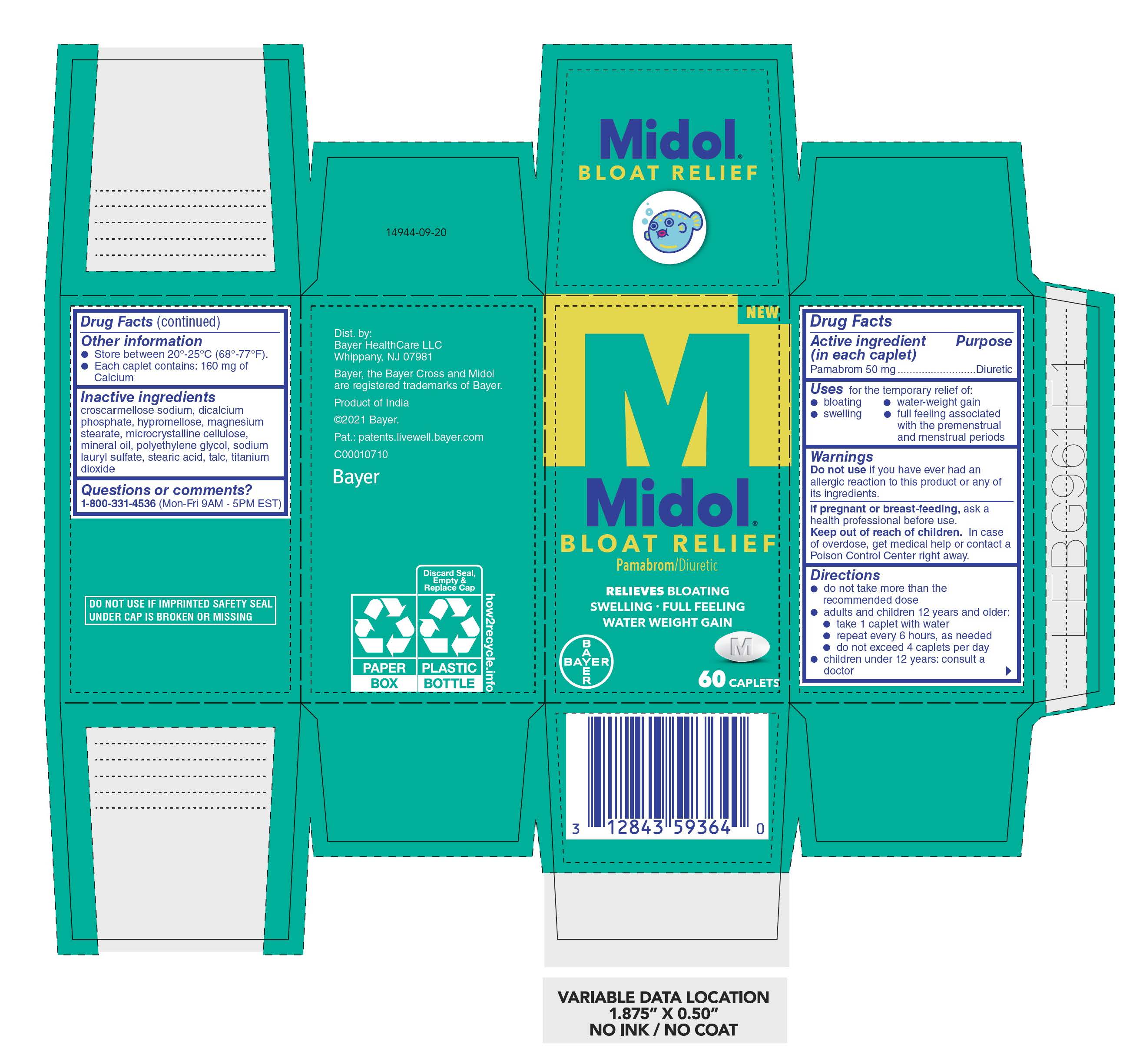 DRUG LABEL: Midol Bloat Relief
NDC: 0280-0070 | Form: TABLET
Manufacturer: Bayer HealthCare LLC.
Category: otc | Type: HUMAN OTC DRUG LABEL
Date: 20251204

ACTIVE INGREDIENTS: PAMABROM 50 mg/1 1
INACTIVE INGREDIENTS: TALC; CROSCARMELLOSE SODIUM; HYPROMELLOSES; MICROCRYSTALLINE CELLULOSE; STEARIC ACID; TITANIUM DIOXIDE; POLYETHYLENE GLYCOL, UNSPECIFIED; MINERAL OIL; SODIUM LAURYL SULFATE; MAGNESIUM STEARATE; DIBASIC CALCIUM PHOSPHATE DIHYDRATE

Midol Boat Relief UI1614837

Drug Facts

Active ingredient (in each caplet) Purpose

Pamabrom 50 mg……….……………………………………….…...Diuretic

INDICATIONS AND USAGE

Uses for the temporary relief of:

• bloating

• water-weight gain

• swelling

• full feeling associated with the premenstrual and menstrual periods

Warnings

Do not use if you have ever had an allergic reaction to this product or any of its ingredients

PREGNANCY OR BREAST FEEDING

If pregnant or breast-feeding, ask a health professional before use

Keep out of reach of children. In case of overdose, get medical help or contact a Poison Control Center right away.

Directions

- do not take more than the recommended dose
- adults and children 12 years and older:
  - take 1 caplet with water
  - repeat every 6 hours, as needed
  - do not exceed 4 caplets per day
- children under 12 years: consult a doctor

Other information

- Store between 20°-25°C (68°-77°F).
- Each caplet contains: 160 mg of Calcium

Inactive ingredients

croscarmellose sodium, dicalcium phosphate, hypromellose, magnesium stearate, microcrystalline cellulose, mineral oil, polyethylene glycol, sodium lauryl sulfate, stearic acid, talc, titanium dioxide

Questions or comments? 1-800-331-4536 (Mon-Fri 9AM - 5PM EST)

Carton 60 count

NEW

Midol®

Bloat Rlief

Pamabrom/Diuretic

RELIEVES BLOATING

SWELLING - FULL FEELING

WATER WEIGHT GAIN

60 CAPLETS